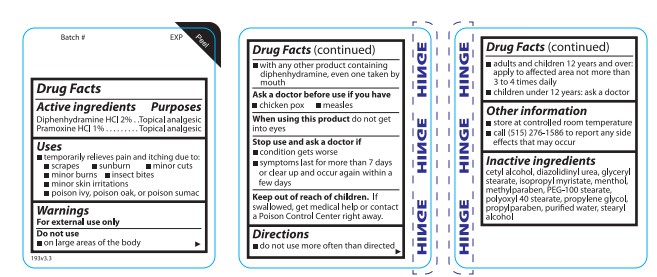 DRUG LABEL: Bite and Itch
NDC: 11383-192 | Form: LOTION
Manufacturer: Weeks & Leo Co., Inc.
Category: otc | Type: HUMAN OTC DRUG LABEL
Date: 20241203

ACTIVE INGREDIENTS: PRAMOXINE HYDROCHLORIDE 1 g/100 mL; DIPHENHYDRAMINE HYDROCHLORIDE 2 g/100 mL
INACTIVE INGREDIENTS: STEARYL ALCOHOL; MENTHOL; METHYLPARABEN; WATER; ISOPROPYL MYRISTATE; GLYCERYL STEARATE/PEG-100 STEARATE; PEG-40 GLYCERYL STEARATE; CETYL ALCOHOL; PROPYLENE GLYCOL; DIAZOLIDINYL UREA; PROPYLPARABEN

Bite and Itch Lotion

Active ingredients

Diphenhydramine HCl 2%

Pramoxine HCl 1%

Purposes

Topical analgesic

Topical analgesic

Uses

Temporarily relieves pain and itching due to:

- scrapes
- sunburn
- minor cuts
- minor burns
- insect bites
- minor skin irritations
- poison ivy, poison oak, or poison sumac

Directions

- do not use more often than directed
- adults and children 12 years and over: apply to affected area not more than 3 to 4 times daily
- children under 12 years: ask a doctor

Warnings

For external use only

Do not use

- on large areas of the body
- with any other product containing diphenhydramine, even one taken by mouth

Ask a doctor before use if you have

- chicken pox
- measles

When using this product do not get into eyes

Stop use and ask a doctor if

- condition gets worse
- symptoms last for more than 7 days or clear up and occur again within a few days

Keep out of reach of children. If swallowed, get medical help or contact a Poison Control Center right away.

Do not use

- on large areas of the body
- with any other product containing diphynhydramine, even one taken by mouth

Ask a doctor before use if you have

- chicken pox
- measles

When using this product do not get into eyes

Stop use and ask a doctor if

- conditions get worse
- symptoms last for more than 7 days or clear up and occur again within a few days

Keep out of reach of children. If swallowed, get medical help or contact a Poison Control Center right away.

Other information

- store at controlled room temperature
- call (515) 276-1586 to report any side effects that may occur

Inactive ingredients

cetyl alcohol, diazolidinyl urea, glyceryl stearate, isopropyl myristate, menthol, methylparaben, PEG-100 stearate, polyoxyl 40 stearate, propylene glycol, propylparaben, purified water, stearyl alcohol

Directions

- do not use more often than directed
- adults and children 12 years and over: apply to affected area not more than 3 to 4 times daily
- children under 12 years: ask a doctor

RECENT MAJOR CHANGES

Added Dosage and Administration section

Updated Warnings section

PACKAGE LABEL

Bite and Itch

Lotion

Pramoxine HCl 1%

Topical Anesthetic

Diphenhydramine HCl 2%

Antihistamine

Pain Relieving Lotion

4 Fl Oz (118 mL)